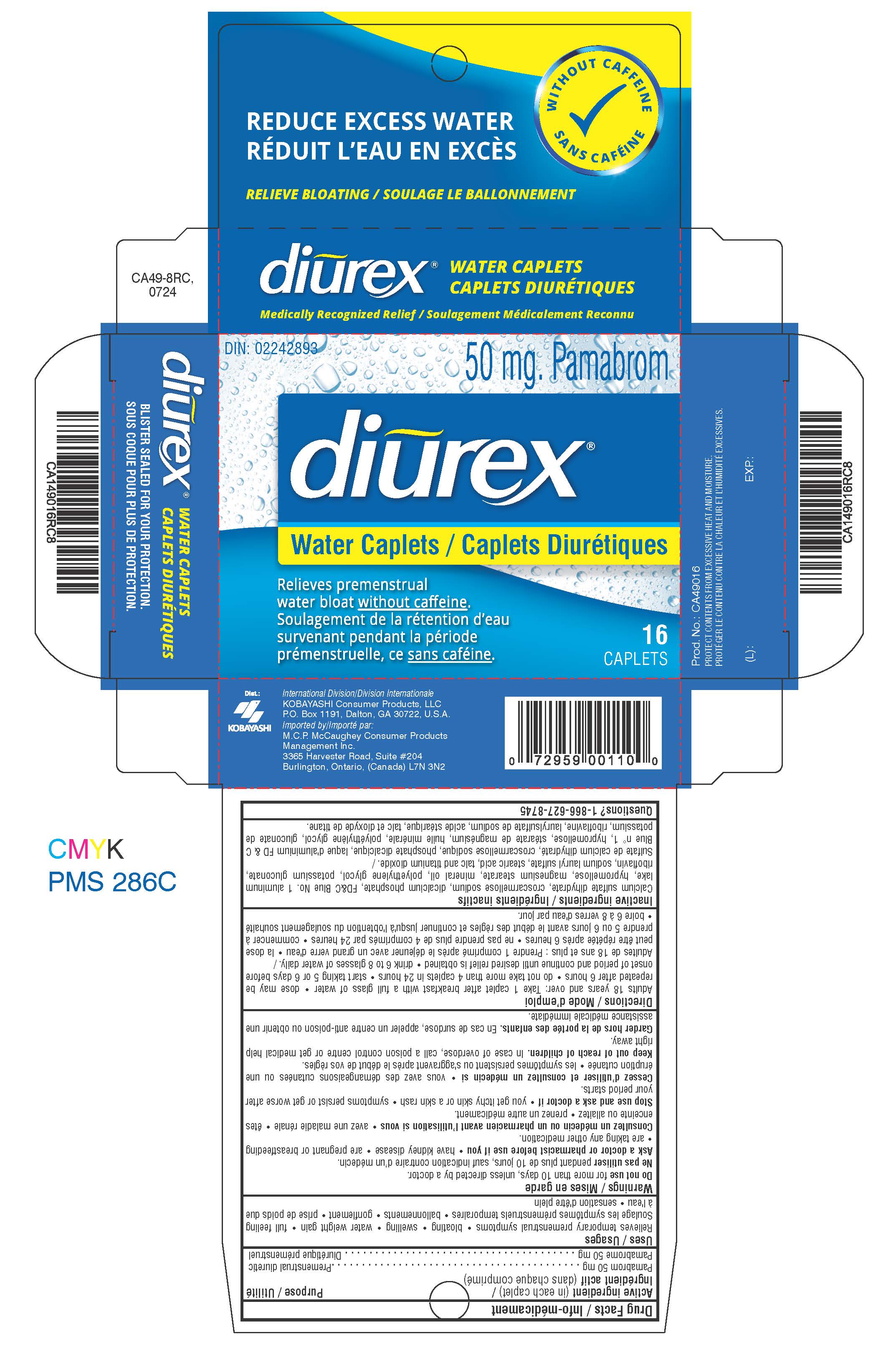 DRUG LABEL: Diurex
NDC: 52389-349 | Form: TABLET, FILM COATED
Manufacturer: Kobayashi Healthcare International, Inc.
Category: otc | Type: HUMAN OTC DRUG LABEL
Date: 20250507

ACTIVE INGREDIENTS: PAMABROM 50 mg/1 1
INACTIVE INGREDIENTS: CROSCARMELLOSE SODIUM; DIBASIC CALCIUM PHOSPHATE DIHYDRATE; FD&C BLUE NO. 1; HYPROMELLOSES; MAGNESIUM STEARATE; LIGHT MINERAL OIL; POLYETHYLENE GLYCOL 400; CALCIUM SULFATE DIHYDRATE; POTASSIUM GLUCONATE; RIBOFLAVIN; SODIUM LAURYL SULFATE; STEARIC ACID; TITANIUM DIOXIDE; TALC

Canadian Diurex Water Caplets